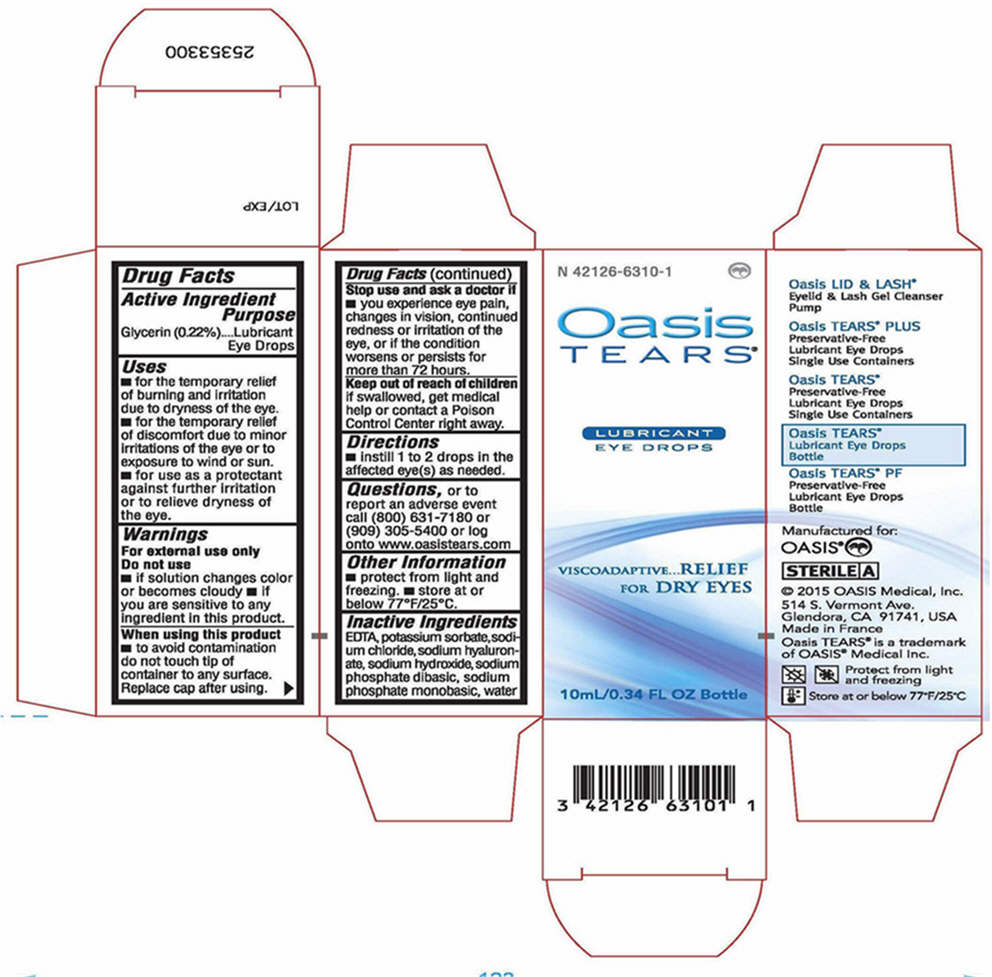 DRUG LABEL: OASIS Tears
NDC: 42126-6310 | Form: SOLUTION/ DROPS
Manufacturer: OASIS Medical, Inc.
Category: otc | Type: HUMAN OTC DRUG LABEL
Date: 20250122

ACTIVE INGREDIENTS: GLYCERIN 2 g/1000 mL
INACTIVE INGREDIENTS: HYALURONATE SODIUM; SODIUM CHLORIDE; SODIUM PHOSPHATE, MONOBASIC, UNSPECIFIED FORM; SODIUM PHOSPHATE, DIBASIC, UNSPECIFIED FORM; POTASSIUM SORBATE; EDETATE DISODIUM; WATER; SODIUM HYDROXIDE

OASIS Tears®
Lubricant Eye Drops

Drug Facts

Active Ingredients

Glycerin (0.22%)

Purpose

lubricant Eye Drops

Uses

- For the temporary relief of burning and irritation due to dryness of the eye
- For the temporary relief of discomfort due to minor irritations of the eye or to exposure to wind or sun
- For use as a protectant against further irritation or to relieve dryness of the eye

Warnings

For external use only

Do not use

- If solution changes color or becomes cloudy
- If you are sensitive to any ingredient in this product

When using this product

- To avoid contamination do not touch tip of container to any surface
- Replace cap after using

Stop use and ask a doctor if

You experience eye pain, changes in vision, continued redness or irritation of the eye, or if the condition worsens or persists for more than 72 hours

Keep out of reach of children. If swallowed, get medical help or contact a Poison Control Center right away.

Directions

Instill 1 or 2 drops in the affected eye(s) as needed.

Questions, or to report an adverse event call:

(800) 631-7180 or (909) 305-5400 or log onto www.oasistears.com

Other information

- Protect from light and freezing
- Store at or below 77°F/25°C

Inactive Ingredients

EDTA, potassium sorbate, sodium chloride, sodium hyaluronate, sodium hydroxide, sodium phosphate dibasic, sodium phosphate monobasic, water

PRINCIPAL DISPLAY PANEL - 10mL Bottle Carton

Oasis
TEARS ®

LUBRICANT EYE DROPS

VISCOADAPTIVE...RELIEF
FOR DRY EYES

10mL/0.3 fl. oz.